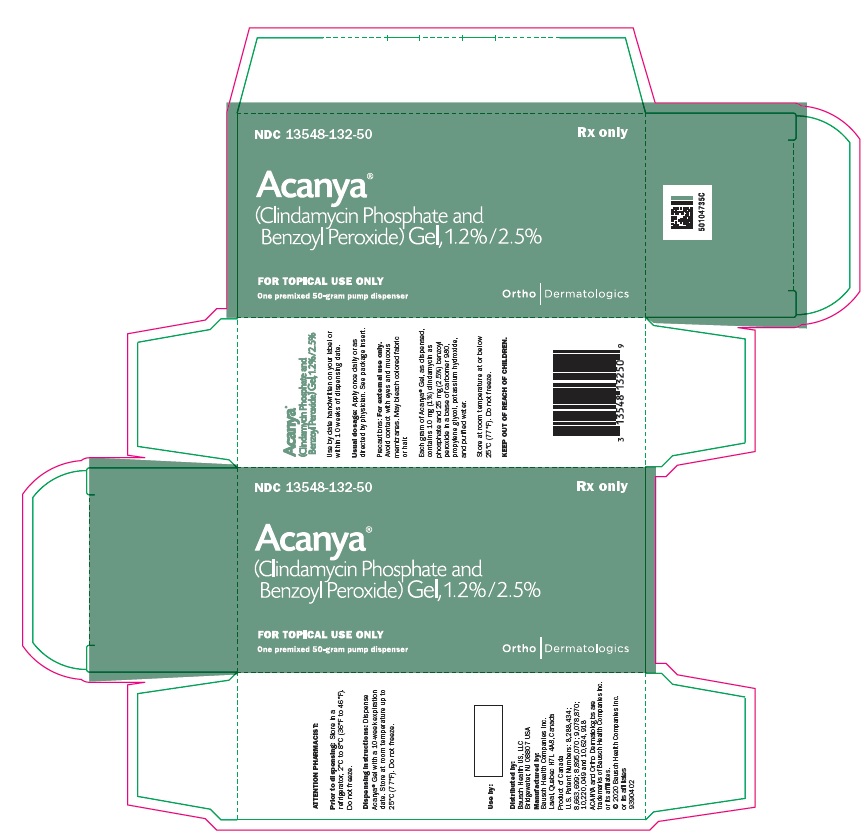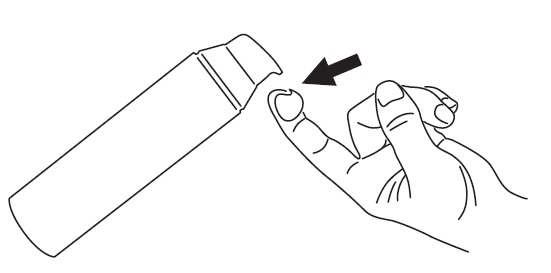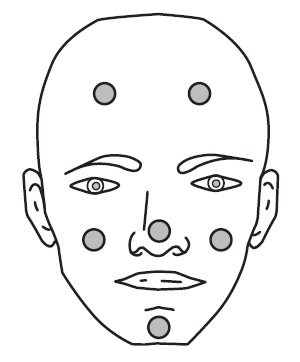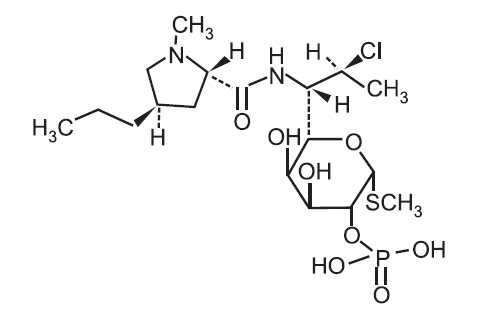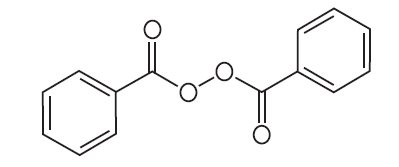 DRUG LABEL: Acanya
NDC: 13548-132 | Form: GEL
Manufacturer: Bausch Health US, LLC
Category: prescription | Type: HUMAN PRESCRIPTION DRUG LABEL
Date: 20200930

ACTIVE INGREDIENTS: Clindamycin Phosphate 10 mg/1 g; Benzoyl Peroxide 25 mg/1 g
INACTIVE INGREDIENTS: Water; CARBOMER HOMOPOLYMER TYPE C (ALLYL PENTAERYTHRITOL CROSSLINKED); propylene glycol; potassium hydroxide

HIGHLIGHTS OF PRESCRIBING INFORMATION

These highlights do not include all the information needed to use ACANYA Gel safely and effectively. See full prescribing information for ACANYA Gel.
ACANYA®
(clindamycin phosphate and benzoyl peroxide) gel, for topical use
Initial U.S. Approval: 2000

1 INDICATIONS AND USAGE

ACANYA Gel is a combination of clindamycin phosphate (a lincosamide antibacterial) and benzoyl peroxide indicated for the topical treatment of acne vulgaris in patients 12 years or older. (1)

2 DOSAGE AND ADMINISTRATION

- Apply a pea-sized amount of ACANYA Gel to the face once daily. (2)
- Not for oral, ophthalmic, or intravaginal use. (2)

3 DOSAGE FORMS AND STRENGTHS

Gel, 1.2% clindamycin phosphate/2.5% benzoyl peroxide

4 CONTRAINDICATIONS

ACANYA Gel is contraindicated in:

- Patients who have demonstrated hypersensitivity (e.g., anaphylaxis) to clindamycin, benzoyl peroxide, any components of the formulation, or lincomycin. (4.1)
- Patients with a history of regional enteritis, ulcerative colitis, or antibiotic-associated colitis. (4.2)

5 WARNINGS AND PRECAUTIONS

- Colitis: Orally and parenterally administered clindamycin has been associated with severe colitis, which may result in death. Diarrhea, bloody diarrhea, and colitis (including pseudomembranous colitis) have been reported with the use of topical and systemic clindamycin. ACANYA Gel should be discontinued if significant diarrhea occurs. (5.1)
- Ultraviolet Light and Environmental Exposure: Minimize sun exposure following drug application. (5.2)

6 ADVERSE REACTIONS

The following selected adverse reactions occurred in less than 0.2% of patients: application site pain (0.1%); application site exfoliation (0.1%); and application site irritation (0.1%). (6.1)

To report SUSPECTED ADVERSE REACTIONS, contact Bausch Health US, LLC at 1-800-321-4576 or FDA at 1-800-FDA-1088 or www.fda.gov/medwatch.

7 DRUG INTERACTIONS

- Avoid using ACANYA Gel in combination with topical or oral erythromycin-containing products because of its clindamycin component. (7.1)

FULL PRESCRIBING INFORMATION

1 INDICATIONS AND USAGE

ACANYA® Gel is indicated for the topical treatment of acne vulgaris in patients 12 years or older.

2 DOSAGE AND ADMINISTRATION

Before applying ACANYA Gel, wash your face gently with a mild soap, rinse with warm water, and pat your skin dry.

Apply a pea-sized amount of ACANYA Gel to the face once daily. Avoid the eyes, mouth, mucous membranes, or areas of broken skin.

Use of ACANYA Gel beyond 12 weeks has not been evaluated.

Concomitant topical acne therapy should be used with caution because a possible cumulative irritancy effect may occur, especially with the use of peeling, desquamating, or abrasive agents.

ACANYA Gel is not for oral, ophthalmic, or intravaginal use.

3 DOSAGE FORMS AND STRENGTHS

Gel, 1.2%/2.5%

Each gram of ACANYA Gel contains 10 mg (1%) clindamycin as phosphate, and 25 mg (2.5%) benzoyl peroxide in a white to off-white, opaque, smooth gel.

4 CONTRAINDICATIONS

4.1 Hypersensitivity

ACANYA Gel is contraindicated in those individuals who have shown hypersensitivity to clindamycin, benzoyl peroxide, any components of the formulation, or lincomycin. Anaphylaxis, as well as allergic reactions leading to hospitalization, has been reported in postmarketing use with ACANYA Gel [see Postmarketing Experience (6.2)].

4.2 Colitis/Enteritis

ACANYA Gel is contraindicated in patients with a history of regional enteritis, ulcerative colitis, or antibiotic-associated colitis [see Warnings and Precautions (5.1)].

5 WARNINGS AND PRECAUTIONS

5.1 Colitis

Systemic absorption of clindamycin has been demonstrated following topical use of clindamycin. Diarrhea, bloody diarrhea, and colitis (including pseudomembranous colitis) have been reported with the use of topical and systemic clindamycin. When significant diarrhea occurs, ACANYA Gel should be discontinued.

Severe colitis has occurred following oral and parenteral administration of clindamycin with an onset of up to several weeks following cessation of therapy. Antiperistaltic agents such as opiates and diphenoxylate with atropine may prolong and/or worsen severe colitis. Severe colitis may result in death.

Studies indicate toxin(s) produced by Clostridia is one primary cause of antibiotic-associated colitis. The colitis is usually characterized by severe persistent diarrhea and severe abdominal cramps and may be associated with the passage of blood and mucus. Stool cultures for Clostridium difficile and stool assay for C. difficile toxin may be helpful diagnostically.

5.2 Ultraviolet Light and Environmental Exposure

Minimize sun exposure including use of tanning beds or sun lamps following drug application.

5.3 Concomitant Topical Medications

Concomitant topical acne therapy should be used with caution since a possible cumulative irritancy effect may occur, especially with the use of peeling, desquamating, or abrasive agents. If irritancy or dermatitis occurs, reduce frequency of application or temporarily interrupt treatment and resume once the irritation subsides. Treatment should be discontinued if the irritation persists.

6 ADVERSE REACTIONS

6.1 Clinical Trials Experience

Because clinical trials are conducted under widely varying conditions, adverse reactions observed in the clinical trials of a drug cannot always be directly compared to rates in the clinical trials of another drug and may not reflect the rates observed in practice.

The following selected adverse reactions occurred in less than 0.2% of subjects treated with ACANYA Gel: application site pain (0.1%); application site exfoliation (0.1%); and application site irritation (0.1%).

During clinical trials, subjects were assessed for local cutaneous signs and symptoms of erythema, scaling, itching, burning and stinging. Most local skin reactions increased and peaked around Week 4 and continually decreased over time reaching near baseline levels by Week 12. The percentage of subjects that had symptoms present before treatment, the maximum value recorded during treatment, and the percent with symptoms present at Week 12 are shown in Table 1.

Table 1: Percent of Subjects with Local Skin Reactions. Combined Results from the Two Phase 3 Trials (N = 773)
 | Before Treatment (Baseline) |  |  | Maximum During Treatment |  |  | End of Treatment (Week 12)
 | Mild | Mod.* | Severe | Mild | Mod.* | Severe | Mild | Mod.* | Severe
Erythema | 22 | 4 | 0 | 25 | 5 | < 1 | 15 | 2 | 0
Scaling | 8 | < 1 | 0 | 18 | 3 | 0 | 8 | 1 | 0
Itching | 10 | 2 | 0 | 15 | 2 | 0 | 6 | < 1 | 0
Burning | 3 | < 1 | 0 | 8 | 2 | 0 | 2 | < 1 | 0
Stinging | 2 | < 1 | 0 | 6 | 1 | 0 | 1 | < 1 | 0

6.2 Postmarketing Experience

Because these reactions are reported voluntarily from a population of uncertain size, it is not always possible to reliably estimate their frequency or establish a causal relationship to drug exposure.

Anaphylaxis, as well as allergic reactions leading to hospitalizations, has been reported in postmarketing use of products containing clindamycin/benzoyl peroxide.

7 DRUG INTERACTIONS

7.1 Erythromycin

ACANYA Gel should not be used in combination with topical or oral erythromycin-containing products due to its clindamycin component. In vitro studies have shown antagonism between erythromycin and clindamycin. The clinical significance of this in vitro antagonism is not known.

7.2 Neuromuscular Blocking Agents

Clindamycin has been shown to have neuromuscular blocking properties that may enhance the action of other neuromuscular blocking agents. Therefore, ACANYA Gel should be used with caution in patients receiving such agents.

8 USE IN SPECIFIC POPULATIONS

8.1 Pregnancy

Risk Summary

There are no available data on ACANYA Gel use in pregnant women to evaluate a drug-associated risk of major birth defects, miscarriage, or adverse maternal or fetal outcomes. The limited published data on use of clindamycin in pregnant women with exposure during the first trimester are insufficient to inform a drug-associated risk of pregnancy-related adverse outcomes (see Data).In limited published clinical trials with pregnant women, the systemic administration of clindamycin during the second and third trimesters has not been associated with an increased frequency of major birth defects.

In animal reproduction studies, clindamycin did not cause malformations or embryo-fetal development toxicity in pregnant rats and mice when administered during the period of organogenesis at systemic doses up to 240 times the maximum recommended human dose (MRHD) of 2.5 g ACANYA Gel, based on body surface area (BSA) comparisons (see Data).

The estimated background risk of major birth defects and miscarriage for the indicated population is unknown. All pregnancies have a background risk of major birth defects, loss, and other adverse outcomes. In the U.S. general population, the estimated background risk of major birth defects and miscarriage in clinically recognized pregnancies is 2-4% and 15-20%, respectively.

Data

Human Data

In limited published trials in pregnant women administered clindamycin during the first trimester of pregnancy, there was no difference in the rate of major birth defects reported among in utero exposed infants compared to unexposed infants. These data cannot definitely establish or exclude any clindamycin-associated risk during pregnancy.

Animal Data

Animal reproductive/developmental toxicity studies have not been conducted with ACANYA Gel or benzoyl peroxide. Developmental toxicity studies of clindamycin performed in pregnant rats and mice administered during the period of organogenesis at oral doses of up to 600 mg/kg/day (240 and 120 times the MRHD for, respectively, based on BSA comparisons) or subcutaneous doses of up to 200 mg/kg/day (80 and 40 times the MRHD for clindamycin, respectively, based on BSA comparisons) revealed no malformations or embryo-fetal development toxicity.

8.2 Lactation

Risk Summary

There are no data on the presence of clindamycin or benzoyl peroxide in human milk, the effects on the breastfed child, or the effects on milk production following topical administration. However, clindamycin has been reported to be present in breast milk in small amounts following oral and parenteral administration. The developmental and health benefits of breastfeeding should be considered along with the mother’s clinical need for ACANYA Gel and any potential adverse effects on the breastfed child from ACANYA Gel or from the underlying maternal condition.

Clinical Considerations

If used during lactation and ACANYA Gel is applied to the chest, care should be taken to avoid accidental ingestion by the infant.

8.4 Pediatric Use

Safety and effectiveness of ACANYA Gel in pediatric patients under the age of 12 have not been evaluated.

8.5 Geriatric Use

Clinical trials of ACANYA Gel did not include sufficient numbers of subjects aged 65 and older to determine whether they respond differently from younger subjects.

11 DESCRIPTION

ACANYA (clindamycin phosphate and benzoyl peroxide) Gel, 1.2%/2.5% is a combination product with two active ingredients in a white to off-white, opaque, smooth, aqueous gel formulation intended for topical use. Clindamycin phosphate is a water-soluble ester of the semisynthetic antibiotic produced by a 7(S)-chloro-substitution of the 7(R)‑hydroxyl group of the parent antibiotic lincomycin.

The chemical name for clindamycin phosphate is Methyl 7-chloro-6,7,8-trideoxy-6-(1-methyl-trans-4-propyl-L-2-pyrrolidinecarboxamido)-1-thio-L-threo-α-D-galacto-octopyranoside 2-(dihydrogen phosphate). The structural formula for clindamycin phosphate is represented below:

Clindamycin phosphate:

Molecular Formula: C18H34ClN2O8PS Molecular Weight: 504.97

Benzoyl peroxide is an antibacterial and keratolytic agent. The structural formula for benzoyl peroxide is represented below:

Benzoyl peroxide:

Molecular Formula: C14H10O4 Molecular Weight: 242.23

ACANYA Gel contains the following inactive ingredients: carbomer 980, potassium hydroxide, propylene glycol, and purified water. Each gram of ACANYA Gel contains 1.2% of clindamycin phosphate which is equivalent to 1% clindamycin.

12 CLINICAL PHARMACOLOGY

12.1 Mechanisms of Action

Clindamycin: Clindamycin is a lincosamide antibacterial [see Microbiology (12.4)].

Benzoyl Peroxide: Benzoyl peroxide is an oxidizing agent with bactericidal and keratolytic effects but the precise mechanism of action is unknown.

12.3 Pharmacokinetics

The systemic absorption of clindamycin was investigated in an open-label, multiple-dose trial in 16 adult subjects with moderate to severe acne vulgaris treated with 1 gram of ACANYA Gel applied to the face once daily for 30 days. Twelve subjects (75%) had at least one quantifiable clindamycin plasma concentration above the lower limit of quantification (LOQ = 0.5 ng/mL) on Day 1 or Day 30. On Day 1, the mean (± standard deviation) peak plasma concentration (Cmax) was 0.78 ± 0.22 ng/mL (n=9 with measurable concentrations), and the mean AUC0-t was 5.29 ± 0.81 h.ng/mL (n=4). On Day 30, the mean Cmax was 1.22 ± 0.88 ng/mL (n=10), and the mean AUC0-t was 8.42 ± 6.01 h.ng/mL (n=6). Clindamycin plasma concentrations were below LOQ in all subjects at 24 hours post-dose on the three tested days (Day 1, 15, and 30).

Benzoyl peroxide has been shown to be absorbed by the skin where it is converted to benzoic acid.

12.4 Microbiology

Clindamycin binds to the 50S ribosomal subunits of susceptible bacteria and prevents elongation of peptide chains by interfering with peptidyl transfer, thereby suppressing bacterial protein synthesis.

Clindamycin and benzoyl peroxide individually have been shown to havein vitro activity against Propionibacterium acnes, an organism which has been associated with acne vulgaris; however, the clinical significance of this activity against P. acnes is not known.

P. acnes resistance to clindamycin has been documented. Resistance to clindamycin is often associated with resistance to erythromycin.

13 NONCLINICAL TOXICOLOGY

13.1 Carcinogenesis, Mutagenesis, Impairment of Fertility

Carcinogenicity, mutagenicity, and impairment of fertility testing of ACANYA Gel have not been performed.

Benzoyl peroxide has been shown to be a tumor promoter and progression agent in a number of animal studies. Benzoyl peroxide in acetone at doses of 5 and 10 mg administered topically twice per week for 20 weeks induced skin tumors in transgenic Tg.AC mice. The clinical significance of this is unknown.

Carcinogenicity studies have been conducted with a gel formulation containing 1% clindamycin and 5% benzoyl peroxide. In a 2-year dermal carcinogenicity study in mice, treatment with the gel formulation at doses of 900, 2700, and 15000 mg/kg/day (1.8, 5.4, and 30 times the MRHD for clindamycin and 3.6, 10.8, and 60 times the MRHD for benzoyl peroxide, respectively, based on BSA comparisons) did not cause any increase in tumors. However, topical treatment with a different gel formulation containing 1% clindamycin and 5% benzoyl peroxide at doses of 100, 500, and 2000 mg/kg/day caused a dose-dependent increase in the incidence of keratoacanthoma at the treated skin site of male rats in a 2-year dermal carcinogenicity study in rats. In an oral (gavage) carcinogenicity study in rats, treatment with the gel formulation at doses of 300, 900, and 3000 mg/kg/day (1.2, 3.6, and 12 times the MRHD for clindamycin and 2.4, 7.2, and 24 times the MRHD for benzoyl peroxide, respectively, based on BSA comparisons) for up to 97 weeks did not cause any increase in tumors.

Clindamycin phosphate was not genotoxic in the human lymphocyte chromosome aberration assay. Benzoyl peroxide has been found to cause DNA strand breaks in a variety of mammalian cell types, to be mutagenic in S. typhimurium tests by some but not all investigators, and to cause sister chromatid exchanges in Chinese hamster ovary cells.

Fertility studies have not been performed with ACANYA Gel or benzoyl peroxide, but fertility and mating ability have been studied with clindamycin. Fertility studies in rats treated orally with up to 300 mg/kg/day of clindamycin (approximately 120 times the MRHD for clindamycin, based on BSA comparisons) revealed no effects on fertility or mating ability.

14 CLINICAL STUDIES

The safety and efficacy of once daily use of ACANYA Gel were assessed in two 12-week multi-center, randomized, blinded trials in subjects 12 years and older with moderate to severe acne vulgaris. The two trials were identical in design and compared ACANYA Gel to clindamycin in the vehicle gel, benzoyl peroxide in the vehicle gel, and the vehicle gel alone.

The co-primary efficacy variables were:

1. Mean absolute change from baseline at Week 12 in:
2. Inflammatory lesion counts
3. Non-inflammatory lesion counts
4. Percent of subjects who had a 2-grade improvement from baseline on an Evaluator’s Global Severity (EGS) score.

The EGS scoring scale used in all of the clinical trials for ACANYA Gel is as follows:

Grade | Description
Clear | Normal, clear skin with no evidence of acne vulgaris
Almost Clear | Rare non-inflammatory lesions present, with rare non-inflamed papules (papules must be resolving and may be hyperpigmented, though not pink-red)
Mild | Some non-inflammatory lesions are present, with few inflammatory lesions (papules/pustules only; no nodulocystic lesions)
Moderate | Non-inflammatory lesions predominate, with multiple inflammatory lesions evident: several to many comedones and papules/pustules, and there may or may not be one small nodulocystic lesion
Severe | Inflammatory lesions are more apparent, many comedones and papules/pustules, there may or may not be a few nodulocystic lesions
Very Severe | Highly inflammatory lesions predominate, variable number of comedones, many papules/pustules and many nodulocystic lesions

The results of Trial 1 at Week 12 are presented in Table 2:

Table 2: Trial 1 Results
 | ACANYA Gel | Clindamycin Gel | Benzoyl Peroxide Gel | Vehicle Gel
Trial 1 | N = 399 | N = 408 | N = 406 | N = 201
EGSS Clear or Almost Clear | 115 (29%) | 84 (21%) | 76 (19%) | 29 (14%)
2-grade reduction from baseline | 131 (33%) | 100 (25%) | 96 (24%) | 38 (19%)
Inflammatory Lesions:
Mean absolute change | 14.8 | 12.2 | 13.0 | 9.0
Mean percent (%) reduction | 55.0% | 47.1% | 49.3% | 34.5%
Non-Inflammatory Lesions:
Mean absolute change | 22.1 | 17.9 | 20.6 | 13.2
Mean percent (%) reduction | 45.3% | 38.0% | 40.2% | 28.6%

The results of Trial 2 at Week 12 are presented in Table 3:

Table 3: Trial 2 Results
 | ACANYA Gel | Clindamycin Gel | Benzoyl Peroxide Gel | Vehicle Gel
Trial 2 | N = 398 | N = 404 | N = 403 | N = 194
EGSS Clear or Almost Clear | 113 (28%) | 94 (23%) | 94 (23%) | 21 (11%)
2-grade reduction from baseline | 147 (37%) | 114 (28%) | 114 (28%) | 27 (14%)
Inflammatory Lesions:
Mean absolute change | 13.7 | 11.3 | 11.2 | 5.7
Mean percent (%) reduction | 54.2% | 45.3% | 45.7% | 23.3%
Non-Inflammatory Lesions:
Mean absolute change | 19.0 | 14.9 | 15.2 | 8.3
Mean percent (%) reduction | 41.2% | 34.3% | 34.5% | 19.2%

16 HOW SUPPLIED/STORAGE AND HANDLING

16.1 How Supplied

ACANYA Gel, 1.2%/2.5%, a white to off-white smooth gel is supplied as:

NDC 13548-132-50 50 g pump

16.2 Dispensing Instructions for the Pharmacist

- Dispense ACANYA Gel with a 10-week expiration date.
- Specify “Store at room temperature up to 25°C (77°F). Do not freeze.”

16.3 Storage and Handling

- PHARMACIST: Prior to Dispensing: Store in a refrigerator, 2° to 8°C (36° to 46°F).
- PATIENT: Store at room temperature at or below 25°C (77°F).
- Protect from freezing.
- Store pump upright.
- Keep out of the reach of children.
- Keep container tightly closed.

17 PATIENT COUNSELING INFORMATION

Advise the patient to read the FDA-approved patient labeling (Patient Information).

- Patients who develop allergic reactions such as severe swelling or shortness of breath should discontinue use and contact their physician immediately.
- ACANYA Gel may cause irritation such as erythema, scaling, itching, or burning, especially when used in combination with other topical acne therapies.
- Excessive or prolonged exposure to sunlight should be limited. To minimize exposure to sunlight, a hat or other clothing should be worn. Sunscreen may also be used.
- ACANYA Gel may bleach hair or colored fabric.

Distributed by:
Bausch Health US, LLC
Bridgewater, NJ 08807 USA

Manufactured by:
Bausch Health Companies Inc.
Laval, Quebec H7L 4A8, Canada

U.S. Patent Numbers: 8,288,434; 8,663,699; 8,895,070; 9,078,870; 10,220,049 and 10,624,918

ACANYA is a trademark of Bausch Health Companies Inc. or its affiliates.

© 2020 Bausch Health Companies Inc. or its affiliates

9387203

Patient Package Insert

PATIENT INFORMATION

ACANYA®(AH-CAN΄-YAH)
  (clindamycin phosphate and benzoyl peroxide)
  gel, 1.2%/2.5%

Important information: ACANYA Gel is for use on skin only (topical use). Do not use ACANYA Gel in your mouth, eyes, or vagina.

What is ACANYA Gel?
ACANYA Gel is a prescription medicine used on the skin (topical) to treat acne vulgaris in people 12 years of age and older.
It is not known if ACANYA Gel is safe and effective for use longer than 12 weeks.
It is not known if ACANYA Gel is safe and effective in children under 12 years of age.

Do not use ACANYA Gel if you have:

- had an allergic reaction to clindamycin, benzoyl peroxide, lincomycin or any of the ingredients in ACANYA Gel. See the end of this leaflet for a complete list of ingredients in ACANYA Gel.
- Crohn’s disease or ulcerative colitis.
- had inflammation of the colon (colitis), or severe diarrhea with past antibiotic use.
Talk with your doctor if you are not sure if you have any of the conditions listed above.

Before using ACANYA Gel, tell your doctor about all of your medical conditions, including if you:
2. plan to have surgery. ACANYA Gel may affect how certain medicines work that may be given during
surgery.
4. are pregnant or plan to become pregnant. It is not known if ACANYA Gel will harm your unborn baby.
5. are breastfeeding or plan to breastfeed. It is not known if ACANYA Gel passes into your breast milk. Clindamycin when taken by mouth or by injection has been reported to appear in breast milk. Talk to your doctor about the best way to feed your baby during treatment with ACANYA Gel.

Tell your doctor about all the medicines you take, including prescription and over-the-counter medicines, vitamins and herbal supplements. ACANYA Gel may affect the way other medicines work and other medicines may affect how ACANYA Gel works.

- Especially tell your doctor if you take medicine by mouth that contains erythromycin or use products on your skin that contain erythromycin. ACANYA Gel should not be used with products that contain erythromycin.
- Tell your doctor about any skin products you use. Other skin and topical acne products may increase the irritation of your skin when used with ACANYA Gel.

Know the medicines you take. Keep a list of them and show it to your doctor and pharmacist when you get a new medicine.

How should I use ACANYA Gel?

- Use ACANYA Gel exactly as your doctor tells you to use it. See the detailed “Instructions for Use” for directions about how to apply ACANYA Gel.
- Your doctor will tell you how long to use ACANYA Gel.
- Apply ACANYA Gel to your face 1 time each day.

What should I avoid while using ACANYA Gel?

- Limit your time in sunlight. You should avoid using tanning beds or sunlamps during treatment with ACANYA Gel. If you have to be in sunlight, wear a wide-brimmed hat or other protective clothing, and use sunscreen to cover the treated areas.
- Avoid getting ACANYA Gel in your hair or on colored fabric. ACANYA Gel may bleach hair or colored fabric.

What are possible side effects of ACANYA Gel?

ACANYA Gel can cause serious side effects including:

- Inflammation of the colon (colitis). Stop using ACANYA Gel and call your doctor right away if you have severe stomach (abdominal) cramps, watery diarrhea, or bloody diarrhea during treatment, and within several weeks after treatment with ACANYA Gel.
- Allergic reactions. Stop using ACANYA Gel, call your doctor and get help right away if you have any of the following symptoms during treatment with ACANYA Gel:
- severe itching
- swelling of your face, eyes, lips, tongue or throat
- trouble breathing

The most common side effects of ACANYA Gel include application site pain, application site irritation including redness, itching, burning, and stinging. Stop using ACANYA Gel and call your doctor if you have a skin rash or your skin becomes very red, itchy or swollen. Talk to your doctor about any side effect that bothers you or that does not go away.

These are not all of the possible side effects with ACANYA Gel.

Call your doctor for medical advice about side effects. You may report side effects to FDA at 1-800-FDA-1088.

How should I store ACANYA Gel?

- Store ACANYA Gel at room temperature at or below 77°F (25°C).
- Do not freeze ACANYA Gel.
- Throw away (discard) ACANYA Gel that has passed the expiration date.
- Store pump upright.
- Keep the container tightly closed.

Keep ACANYA Gel and all medicines out of the reach of children.

General information about the safe and effective use of ACANYA Gel.

Medicines are sometimes prescribed for purposes other than those listed in a Patient Information leaflet. Do not use ACANYA Gel for a condition for which it was not prescribed. Do not give ACANYA Gel to other people, even if they have the same condition you have. It may harm them. You can also ask your doctor or pharmacist for information about ACANYA Gel that is written for healthcare professionals.

What are the ingredients in ACANYA Gel?

Active Ingredients: clindamycin phosphate and benzoyl peroxide

Inactive Ingredients: carbomer 980, potassium hydroxide, propylene glycol, and purified water

Distributed by: Bausch Health US, LLC, Bridgewater, NJ 08807 USA

Manufactured by: Bausch Health Companies Inc., Laval, Quebec H7L 4A8, Canada

U.S. Patent Numbers: 8,288,434; 8,663,699; 8,895,070; 9,078,870; 10,220,049 and 10,624,918

ACANYA is a trademark of Bausch Health Companies Inc. or its affiliates.

© 2020 Bausch Health Companies Inc. or its affiliates

For more information about ACANYA Gel, call 1-800-321-4576.

This Patient Information has been approved by the U.S. Food and Drug Administration.

Revised: 09/2020

9387203

Instructions for Use

ACANYA®(AH-CAN΄-YAH)
(clindamycin phosphate and benzoyl peroxide) gel, 1.2%/2.5%

Important Information: ACANYA Gel is for use on skin only (topical use). ACANYA Gel is not for use in your mouth, eyes or vagina.

Read this Instructions for Use before you start using ACANYA Gel and each time you get a refill. There may be new information. This information does not take the place of talking with your doctor about your medical condition or treatment.

- Apply ACANYA Gel to your face 1 time each day as prescribed.
- Before you apply ACANYA Gel, wash your face gently with a mild soap, rinse with warm water, and pat your skin dry.
- To apply ACANYA Gel to your face, use the pump to dispense one pea-sized amount of ACANYA Gel onto your fingertip. See Figure 1.
- One pea-sized amount of ACANYA Gel should be enough to cover your entire face.

Figure 1

- Dot the one pea-sized amount of ACANYA Gel onto six areas of your face (chin, left cheek, right cheek, nose, left forehead, right forehead). See Figure 2.

Figure 2

- Spread the gel over your face and gently rub it in. It is important to spread the gel over your entire face. If your doctor tells you to put ACANYA Gel on other areas of your skin with acne, be sure to ask how much you should use.
- Wash your hands with soap and water after applying ACANYA Gel.

How should I store ACANYA Gel?

- Store ACANYA Gel at room temperature at or below 77°F (25°C).
- Do not freeze ACANYA Gel.
- Throw away (discard) ACANYA Gel that has passed the expiration date.
- Store pump upright.
- Keep the container tightly closed.

Keep ACANYA Gel and all medicines out of the reach of children.

Distributed by: Bausch Health US, LLC, Bridgewater, NJ 08807 USA

Manufactured by: Bausch Health Companies Inc., Laval, Quebec H7L 4A8, Canada

U.S. Patent Numbers: 8,288,434; 8,663,699; 8,895,070; 9,078,870; 10,220,049 and 10,624,918

ACANYA is a trademark of Bausch Health Companies Inc. or its affiliates.

© 2020 Bausch Health Companies Inc. or its affiliates

The Patient Information and Instructions for Use have been approved by the U.S. Food and Drug Administration.

Issued: 09/2020

9387203

PACKAGE/LABEL PRINCIPAL DISPLAY PANEL

NDC 13548-132-50

Rx only

Acanya®
(Clindamycin Phosphate and
Benzoyl Peroxide) Gel, 1.2% /2.5%

FOR TOPICAL USE ONLY

One premixed 50-gram pump dispenser

Ortho Dermatologics